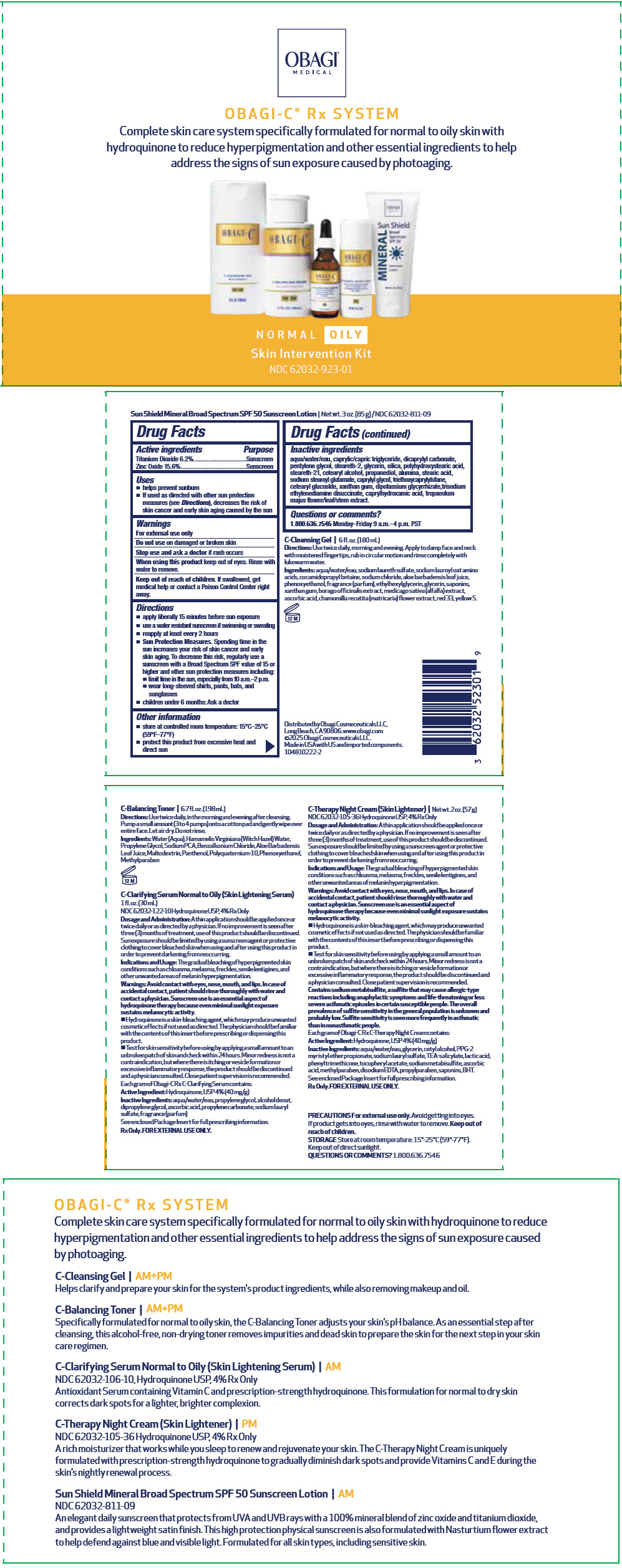 DRUG LABEL: Obagi-C C-Rx system Normal-oily skin Intervention
NDC: 62032-923 | Form: KIT | Route: TOPICAL
Manufacturer: Obagi Cosmeceuticals LLC
Category: otc | Type: HUMAN OTC DRUG LABEL
Date: 20251113

ACTIVE INGREDIENTS: HYDROQUINONE 40 mg/1 mL; HYDROQUINONE 40 mg/1 g; TITANIUM DIOXIDE 6.2 g/100 g; ZINC OXIDE 15.6 g/100 g
INACTIVE INGREDIENTS: PROPYLENE GLYCOL; WATER; ASCORBIC ACID; SODIUM LAURYL SULFATE; PROPYLENE CARBONATE; ALCOHOL; DIPROPYLENE GLYCOL; EDETATE DISODIUM; PPG-2 MYRISTYL ETHER PROPIONATE; TROLAMINE SALICYLATE; SODIUM LAURYL SULFATE; CETYL ALCOHOL; LACTIC ACID, UNSPECIFIED FORM; .ALPHA.-TOCOPHEROL ACETATE; ASCORBIC ACID; SODIUM METABISULFITE; METHYLPARABEN; PROPYLPARABEN; BUTYLATED HYDROXYTOLUENE; PHENYL TRIMETHICONE; GLYCERIN; WATER; ALUMINUM OXIDE; CAPRYLHYDROXAMIC ACID; MEDIUM-CHAIN TRIGLYCERIDES; CAPRYLYL GLYCOL; CETOSTEARYL ALCOHOL; CETEARYL GLUCOSIDE; DICAPRYLYL CARBONATE; GLYCYRRHIZINATE DIPOTASSIUM; GLYCERIN; PENTYLENE GLYCOL; POLYHYDROXYSTEARIC ACID (2300 MW); PROPANEDIOL; SILICON DIOXIDE; SODIUM STEAROYL GLUTAMATE; STEARETH-2; STEARETH-21; STEARIC ACID; TRIETHOXYCAPRYLYLSILANE; TRISODIUM ETHYLENEDIAMINE DISUCCINATE; TROPAEOLUM MAJUS FLOWERING TOP; WATER; XANTHAN GUM

Obagi-C® C-Rx System Normal-Oily Skin Intervention

Drug Facts

ACTIVE INGREDIENT

Active ingredients | Purpose
Titanium Dioxide 6.2% | Sunscreen
Zinc Oxide 15.6% | Sunscreen

Uses

- helps prevent sunburn
- If used as directed with other sun protection measures (see Directions), decreases the risk of skin cancer and early skin aging caused by the sun

Warnings

For external use only

Do not use on damaged or broken skin

Stop use and ask a doctor if rash occurs

When using this product keep out of eyes. Rinse with water to remove.

Keep out of reach of children. If swallowed, get medical help or contact a Poison Control Center right away.

Directions

- apply liberally 15 minutes before sun exposure
- use a water resistant sunscreen if swimming or sweating
- reapply at least every 2 hours
- Sun Protection Measures. Spending time in the sun increases your risk of skin cancer and early skin aging. To decrease this risk, regularly use a sunscreen with a Broad Spectrum SPF value of 15 or higher and other sun protection measures including:
  - limit time in the sun, especially from 10 a.m.–2 p.m.
  - wear long-sleeved shirts, pants, hats, and sunglasses
- children under 6 months: Ask a doctor

Other information

- store at controlled room temperature: 15°C–25°C (59°F–77°F)
- protect this product from excessive heat and direct sun

Inactive ingredients

aqua/water/eau, caprylic/capric triglyceride, dicaprylyl carbonate, pentylene glycol, steareth-2, glycerin, silica, polyhydroxystearic acid, steareth-21, cetearyl alcohol, propanediol, alumina, stearic acid, sodium stearoyl glutamate, caprylyl glycol, triethoxycaprylylsilane, cetearyl glucoslde, xanthan gum, dipotassium glycyrrhizate,trisodium ethylenediamine disuccinate, caprylhydroxamic acid, tropaeolum majus flower/leaf/stem extract.

Questions or comments?

1.800.636.7546 Monday–Friday 9 a.m.–4 p.m. PST

Distributed by Obagi Cosmeceuticals LLC,
Long Beach, CA 90806. www.obagi.com

PRINCIPAL DISPLAY PANEL - Kit Carton

OBAGI®
MEDICAL

OBAGI-C® Rx SYSTEM

Complete skin care system specifically formulated for normal to oily skin with
hydroquinone to reduce hyperpigmentation and other essential ingredients to help
address the signs of sun exposure caused by photoaging.

NORMAL OILY

Skin Intervention Kit

NDC 62032-923-01